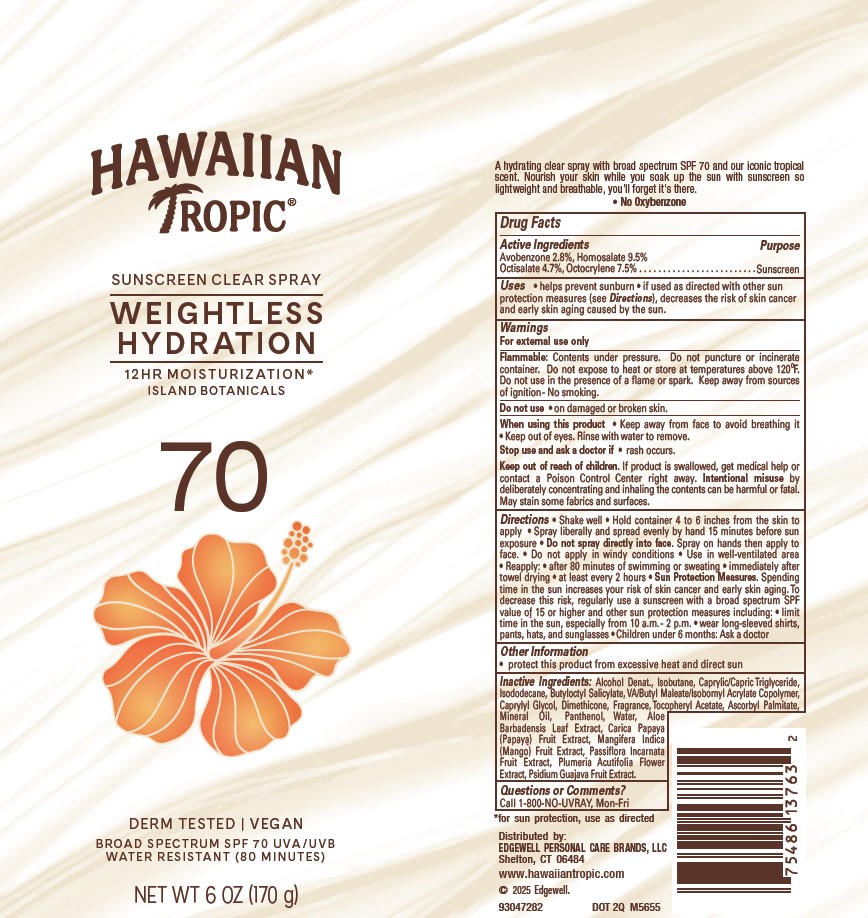 DRUG LABEL: HAWAIIAN TROPIC SUNSCREEN CLEAR WEIGHTLESS HYDRATION SPF70
NDC: 63354-083 | Form: AEROSOL, SPRAY
Manufacturer: Edgewell Personal Care Brands LLC
Category: otc | Type: HUMAN OTC DRUG LABEL
Date: 20251218

ACTIVE INGREDIENTS: HOMOSALATE 9.5 g/100 g; OCTISALATE 4.7 g/100 g; OCTOCRYLENE 7.5 g/100 g; AVOBENZONE 2.8 g/100 g
INACTIVE INGREDIENTS: ISODODECANE; BUTYLOCTYL SALICYLATE; CAPRYLYL GLYCOL; DIMETHICONE; DEHYDRATED ALCOHOL; MEDIUM-CHAIN TRIGLYCERIDES; ALPHA-TOCOPHEROL ACETATE; ASCORBYL PALMITATE; MINERAL OIL; PANTHENOL; WATER; ALOE VERA LEAF; PAPAYA; MANGO; PASSIFLORA INCARNATA FRUIT; PLUMERIA RUBRA FLOWER; GUAVA; ISOBUTANE

Active Ingredients

Avobenzone 2.8%, Homosalate 9.5%, Octisalate 4.7%, Octocrylene 7.5% .

Purpose

Sunscreen

Uses

• helps prevent sunburn • if used as directed with other sun protection measures (see Directions), decreases the risk of skin cancer
and early skin aging caused by the sun.

Warnings

For external use only

Flammable: Contents under pressure. Do not puncture or incinerate container. Do not expose to heat or store at temperatures above 120 F. Do not use in the presence of a flame or spark. Keep away from sources of ignition - No smoking.

Do not use

on damaged or broken skin.

Stop use and ask a doctor

If rash occurs

When using this product

• Keep away from face to avoid breathing it

Keep out of reach of children.

If product is swallowed, get medical help or contact a Poison Control Center right away. Intentional misuse by deliberately concentrating and inhaling the contents can be harmful or fatal. May stain some fabrics and surfaces.

Directions

• Shake well • Hold container 4 to 6 inches from the skin to
apply • Spray liberally and spread evenly by hand 15 minutes before sun
exposure • Do not spray directly into face. Spray on hands then apply to
face. • Do not apply in windy conditions • Use in well-ventilated area
• Reapply: • after 80 minutes of swimming or sweating • immediately after
towel drying • at least every 2 hours • Sun Protection Measures. Spending
time in the sun increases your risk of skin cancer and early skin aging. To
decrease this risk, regularly use a sunscreen with a broad spectrum SPF
value of 15 or higher and other sun protection measures including: • limit
time in the sun, especially from 10 a.m. - 2 p.m. • wear long-sleeved shirts,
pants, hats, and sunglasses • Children under 6 months: Ask a doctor

Other Information

protect this product from excessive heat and direct sun

Inactive Ingredients

Alcohol Denat., Isobutane, Caprylic/Capric Triglyceride, Isododecane, Butyloctyl Salicylate, VA/Butyl Maleate/Isobornyl Acrylate Copolymer, Caprylyl Glycol, Dimethicone, Fragrance, Tocopheryl Acetate, Ascorbyl Palmitate, Mineral Oil, Panthenol, Water, Aloe Barbadensis Leaf Extract, Carica Papaya (Papaya) Fruit Extract, Mangifera Indica (Mango) Fruit Extract, Passiflora Incarnata Fruit Extract, Plumeria Acutifolia Flower Extract, Psidium Guajava Fruit Extract.

Questions or Comments?

Call 1-800-NO-UVRAY, Mon-Fri

PRINCIPAL DISPLAY PANEL

HAWAIIAN

TROPIC

SUNSCREEN CLEAR SPRAY

WEIGHTLESS HYDRATION

12 HR MOISTURIZATION*

ISLAND BOTANICALS

70

DERM TESTED | VEGAN

BROAD SPECTRUM SPF 70 UVA/UVB

WATER RESISTANT (80 MINUTES)

NET WT 6 OZ (170 g)